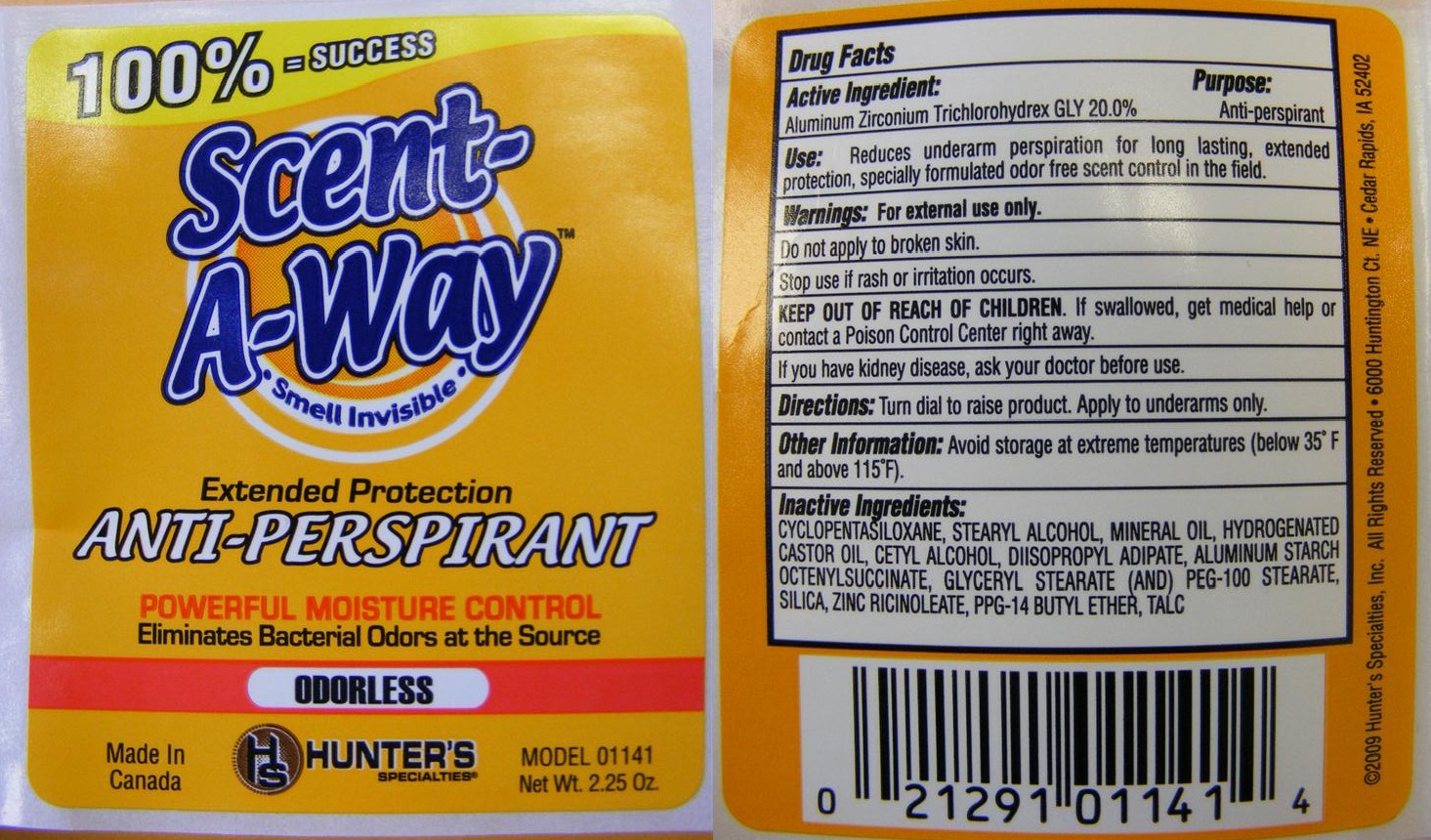 DRUG LABEL: Scent-A-Way Anti-Perspirant
NDC: 63798-696 | Form: STICK
Manufacturer: Hunter's Specialties
Category: otc | Type: HUMAN OTC DRUG LABEL
Date: 20110810

ACTIVE INGREDIENTS: Aluminum Zirconium Trichlorohydrex Gly 20 g/100 g
INACTIVE INGREDIENTS: CYCLOMETHICONE 5; STEARYL ALCOHOL; Mineral Oil; Hydrogenated Castor Oil; DIISOPROPYL ADIPATE; CETYL ALCOHOL; ALUMINUM STARCH OCTENYLSUCCINATE; GLYCERYL MONOSTEARATE; PEG-100 STEARATE; PPG-14 BUTYL ETHER; SILICON DIOXIDE;  ZINC RICINOLEATE ; Talc

Scent-A-Way Extended Protection Anti-Perspirant

Active Ingredient

Aluminum Zirconium Trichlorohydrex 20% (anhydrous)

Purpose

Antiperspirant

Use

Reduces underarm perspiration for long lasting, extended protection, specially formulated odor free scent control in the field.

Warnings

For external use only.

Do not apply to broken skin.

Stop use if rash or irritation occurs.

If you have kidney disease, ask your doctor before use.

Directions

Turn dial to raise product. Apply to underarms only.

Other Information: Avoid storage at extreme temperatures (below 35 F and above 115 F)

Inactive Ingredients
cyclopentasiloxane, stearyl alcohol, mineral oil, hydrogenated castor oil, cetyl alcohol, diisopropyl adipat, aluminum starch octenylsuccinate, glyceryl stearate (and) PEG-100 stearate, silica, zinc ricinoleate, PPG-14 butyl ether, talc

Hunter's Scent-A-Way Label

KEEP OUT OF REACH OF CHILDREN. If swallowed, get medical help or contact a Poison Control Center right away.